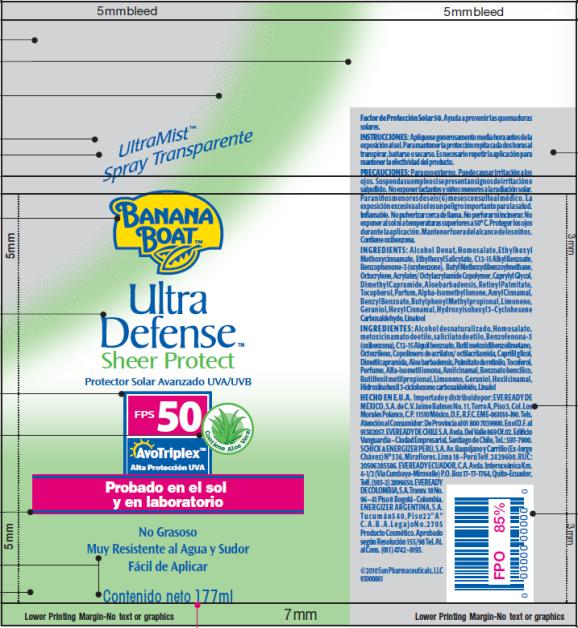 DRUG LABEL: Banana Boat Ultra Defense Sheer Protect FPS 50 LATAM
NDC: 17630-2044 | Form: SPRAY
Manufacturer: Accra-Pac, Inc.
Category: otc | Type: HUMAN OTC DRUG LABEL
Date: 20100422

ACTIVE INGREDIENTS: HOMOSALATE 0.0878 mL/1 mL; OCTINOXATE 0.075 mL/1 mL; OCTISALATE 0.05 mL/1 mL; OCTOCRYLENE 0.025 mL/1 mL; OXYBENZONE 0.05 mL/1 mL; AVOBENZONE 0.03 mL/1 mL
INACTIVE INGREDIENTS: C12-15 ALKYL BENZOATE; CAPRYLYL GLYCOL; ALOE VERA LEAF; VITAMIN A PALMITATE; AMYL CINNAMAL; BENZYL BENZOATE; GERANIOL; LINALOOL, DL-; LIMONENE, (+)-; HEXYL CINNAMALDEHYDE

Banana Boat Ultra Defense Sheer Protect FPS 50 LATAM

Drug Facts

Active Ingredients

Homosalate 0.0878mL / 1mL

Octinoxate 0.075mL / 1mL

Octisalate 0.05mL / 1mL

Octocrylene 0.025mL / 1mL

Oxybenzone 0.05mL / 1mL

Avobenzone 0.03mL / 1mL

INSTRUCCIONES:

Aplíquese generosamente media hora antes de la exposición al sol. Para mantener la protección repita cada dos horas al transpirar, bañarse o secarse. Es necesario repetir la aplicación para mantener la efectividad del producto.

PRECAUCIONES:

Para uso externo. Puede causar irritación a los ojos. Suspenda su empleo si se presentan signos de irritación o salpullido. No exponer lactantes y niños menores a la radiación solar. Para niños menores de seis (6) meses consulte al médico. La exposición excesiva al sol es un peligro importante para la salud. Inflamable. No pulverizar cerca de llama. No perforar ni incinerar. No exponer al sol ni a temperaturas superiores a 50° C. Proteger los ojos durante la aplicación. Mantener fuera del alcance de los niños. Contiene oxibenzona.

INGREDIENTS:

Alcohol Denat, Homosalate, Ethylhexyl Methoxycinnamate, Ethylhexyl Salicylate, C12-15 Alkyl Benzoate, Benzophenone-3 (oxybenzone), Butyl Methoxydibenzoylmethane, Octocrylene, Acrylates/ Octylacrylamide Copolymer, Caprylyl Glycol, Dimethyl Capramide, Aloe barbadensis, Retinyl Palmitate, Tocopherol, Parfum, Alpha-Isomethyl Ionone, Amyl Cinnamal, Benzyl Benzoate, Butylphenyl Methylpropional, Limonene, Geraniol, Hexyl Cinnamal, Hydroxyisohexyl 3-Cyclohexene Carboxaldehyde, Linalool

INGREDIENTES:

Alcohol desnaturalizado, Homosalato, metoxicinamato de etilo, salicilato de etilo, Benzofenona-3 (oxibenzona), C12-15 Alquil benzoato, Butil metoxidibenzoilmetano, Octocrileno, Copolímero de acrilatos/ octilacrilamida, Caprilil glicol, Dimetil capramida, Aloe barbadensis, Palmitato de retinilo, Tocoferol, Perfume, Alfa-isometil ionona, Amil cinamal, Benzoato bencílico, Butilfenil metilpropional, Limoneno, Geraniol, Hexil cinamal, Hidroxiisohexil 3-ciclohexeno carboxaldehído, Linalol

HECHO EN E.U.A.

Importado y distribuido por: EVEREADY DE MÉXICO, S.A. de C.V. Jaime Balmes No. 11, Torre A, Piso 3, Col. Los Morales Polanco, C.P. 11510 México, D.F., R.F.C. EME-861014-J90. Tels. Atención al Consumidor: De Provincia al 01 800 7039900. En el D.F. al 91382057. EVEREADY DE CHILE S.A. Avda. Del Valle 869 Of.02. Edificio Vanguardia – Ciudad Empresarial, Santiago de Chile, Tel.: 597-7900. SCHICK & ENERGIZER PERÚ, S.A. Av. Baquíjano y Carrillo (Ex-Jorge Chávez) N° 336, Miraflores. Lima 18 – Perú Telf. 2429600. RUC: 20506285586. EVEREADY ECUADOR, C.A. Avda. Interoceánica Km. 4-1/2 (Vía Cumbaya-Miravalle) P.O. Box 17-17-1764, Quito-Ecuador, Telf. (593-2) 2899450. EVEREADY DE COLOMBIA, S.A. Transv. 18 No. 96 – 41 Piso 8 Bogotá - Colombia. ENERGIZER ARGENTINA, S.A. Tu c umá n 5 4 0 , P i s o 2 2 " A " C . A . B . A . L e g a j o No . 2 7 0 5 Producto Cosmético. Aprobado según Resolución 155/98 Tel. At. al Cons. (011) 4742 - 8193.

© 2010 Sun Pharmaceuticals, LLC
Manufactured by: Accra Pac, Inc (dba KIK Custom Products)

PRINCIPAL DISPLAY PANEL

UltraMist TM
Spray Transparente
BANANA
BOATTM
Ultra
Defense TM
Sheer Protect
Protector Solar Avanzado UVA/UVB
FPS 50 Contiene Aloe Vera
AvoTriplex TM
Alta Protección UVA
Probado en el sol
y en laboratorio
No Grasoso
Muy Resistente al Agua y Sudor
Fácil de Aplicar
Contenido neto 177ml